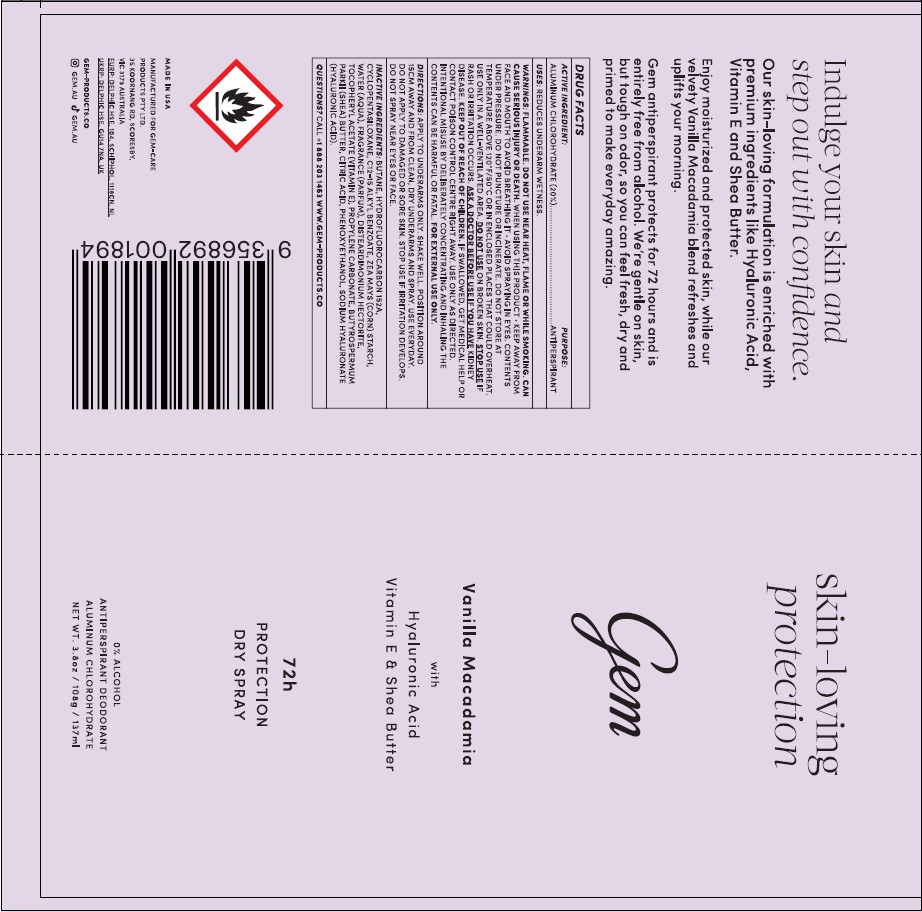 DRUG LABEL: Gem Vanilla Macadamia
NDC: 87190-0050 | Form: AEROSOL, SPRAY
Manufacturer: Gem Products US LLC
Category: otc | Type: HUMAN OTC DRUG LABEL
Date: 20260211

ACTIVE INGREDIENTS: ALUMINUM CHLOROHYDRATE 20 g/100 g
INACTIVE INGREDIENTS: WATER; ZEA MAYS (CORN) STARCH; CYCLOPENTASILOXANE; .ALPHA.-TOCOPHEROL ACETATE; BUTANE; HYDROFLUOROCARBON 152A; PHENOXYETHANOL; CITRIC ACID; DISTEARDIMONIUM HECTORITE; C12-15 ALKYL BENZOATE; SODIUM HYALURONATE; PROPYLENE CARBONATE; BUTYROSPERMUM PARKII (SHEA) BUTTER

Gem Vanilla Macadamia with Hyaluronic Acid Vitamin E & Shea Butter

Drug Facts

ACTIVE INGREDIENT | PURPOSE
ALUMINUM CHLOROHYDRATE (20%) | ANTIPERSPIRANT

PURPOSE

ANTIPERSPIRANT

USES

REDUCES UNDERARM WETNESS

WARNINGS

FLAMMABLE. DO NOT USE NEAR HEAT, FLAME OR WHILE SMOKING. CAN CAUSE SERIOUS INJURY OR DEATH.

WHEN USING THIS PRODUCT KEEP AWAY FROM FACE AND MOUTH TO AVOID BREATHING IT. AVOID SPRAYING IN EYES.

OTHER SAFETY INFORMATION

CONTENTS UNDER PRESSURE. DO NOT PUNCTURE OR INCINERATE. DO NOT STORE AT TEMPERATURE ABOVE 120°F/50°C OR IN ENCLOSED PLACES THAT COULD OVERHEAT. USE ONLY IN A WELL-VENTILATED AREA.

DO NOT USE ON BROKEN SKIN STOP USE IF RASH OR IRRITATION OCCURS.

ASK A DOCTOR BEFORE USE IF YOU HAVE KIDNEY DISEASE.

KEEP OUT OF REACH OF CHILDREN.

OVERDOSAGE

IF SWALLOWED GET MEDICAL HELP OR CONTACT POISON CONTROL CENTER RIGHT AWAY. USE ONLY AS DIRECTED. INTENTATIONAL MISUSE BY DELIBERATELY CONCENTRATING AND INHALING THE CONTENTS CAN BE HARMFUL OR FETAL. FOR EXTERNAL USE ONLY

DIRRECTIONS

APPLY TO UNDERARMS ONLY. SHAKE WELL. POSITION AROUND 15CM AWAY AND FROM CLEAN, DRY UNDERARMS AND SPRAY. USE EVERYDAY. DO NOT APPLY TO DAMAGED OR SORE SKIN. STOP USE IF IRRITATION DEVELOPS. DO NOT SPRAY NEAR EYES OR FACE.

INACTIVE INGREDIENTS

BUTANE, HYDROFLUOROCARBON 152A, CYCLOPENTASILOXANE, C12-15 ALKYL BENZOATE, ZEA M AYS (CORN) STARCH, WATER (AQUA), FRAGRANCE (PARFUM), DISTEARDIM ONIUM HECTORITE, TOCOPHERYLACETATE (VITAM IN E), PROPYLENE CARBONATE, BUTYROSPERMUM PARKII (SHEA) BUTTER, CITRIC ACID, PHENOXYETHANOL, SODIUM HYALURONATE (HYALURONICACID).

QUESTIONS?

CALL + 1-888-203-1463 WWW.GEM-PRODUCTS.CO

PACKAGE LABEL

Gem Vanilla Macadamia NET WT. 3.8oz/108g/137ml